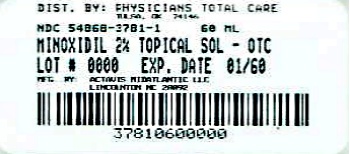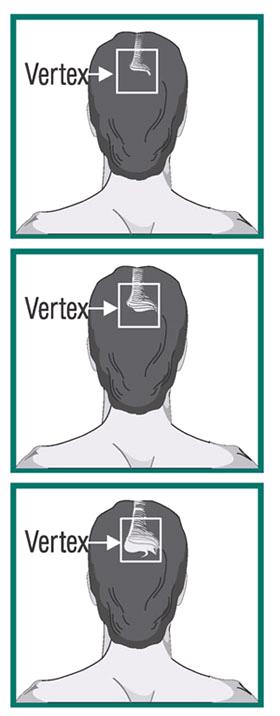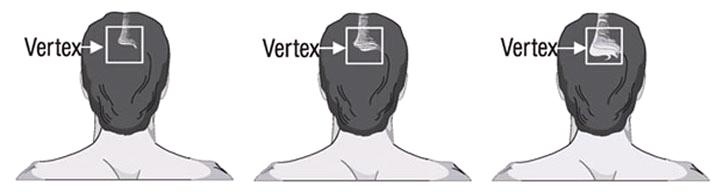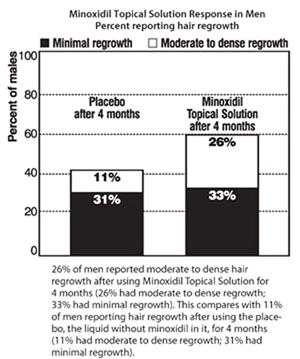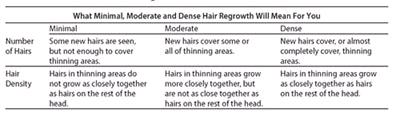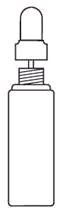 DRUG LABEL: Minoxidil
NDC: 54868-3781 | Form: SOLUTION
Manufacturer: Physicians Total Care, Inc.
Category: otc | Type: HUMAN OTC DRUG LABEL
Date: 20121002

ACTIVE INGREDIENTS: MINOXIDIL 2 g/100 mL
INACTIVE INGREDIENTS: ALCOHOL; PROPYLENE GLYCOL; WATER

Minoxidil Topical Solution 2% (For Men)

ACTIVE INGREDIENT

Minoxidil 2% w/v

PURPOSE

Hair regrowth treatment

USE

To regrow hair on the top of the scalp (vertex only, see pictures on side of carton)

WARNINGS

For external use only

Flammable: Keep away from fire or flame

DO NOT USE IF

- your degree of hair loss is more than that shown on the side of this carton, because this product may not work for you
- you have no family history of hair loss
- your hair loss is sudden and/or patchy
- you do not know the reason for your hair loss
- you are under 18 years of age. Do not use on babies and children.
- your scalp is red, inflamed, infected, irritated, or painful
- you use other medicines on the scalp

ASK A DOCTOR BEFORE USE IF YOU HAVE

Heart disease

WHEN USING THIS PRODUCT

do not apply on other parts of the body

- avoid contact with the eyes. In case of accidental contact, rinse eyes with large amounts of cool tap water.
- some people have experienced changes in hair color and/or texture
- it takes time to regrow hair. You may need to use this product 2 times a day for at least 4 months before you see results.
- the amount of hair regrowth is different for each person. This product will not work for everyone.

STOP USE AND ASK A DOCTOR IF

- chest pain, rapid heartbeat, faintness, or dizziness occurs
- sudden, unexplained weight gain occurs
- your hands or feet swell
- scalp irritation or redness occurs
- unwanted facial hair growth occurs
- you do not see hair regrowth in 4 months

PREGNANCY OR BREAST-FEEDING

May be harmful if used when pregnant or breast-feeding.

KEEP OUT OF REACH OF CHILDREN

If swallowed, get medical help or contact a Poison Control Center right away.

DIRECTIONS

- part your hair and apply one mL 2 times a day directly onto the scalp in the area of hair thinning/loss
- using more or more often will not improve results
- continued use is necessary to increase and keep your hair regrowth, or hair loss will begin again

Other information

- see hair loss pictures on side of this carton
- before use, read all information on carton and enclosed leaflet
- keep this carton. It contains important information.
- in clinical studies of mostly white men aged 18-49 years with moderate degrees of hair loss, the following response to minoxidil topical solution 2% for men was reported: 26% of men reported moderate to dense hair regrowth after using minoxidil topical solution 2% for men for 4 months (26% had moderate to dense regrowth; 33% had minimal regrowth). This compares with 11% of men reporting hair regrowth after using the placebo, the liquid without minoxidil in it, for 4 months (11% had moderate to dense regrowth; 31% had minimal regrowth).
- store at controlled room temperature 20° to 25°C (68° to 77°F). Keep tightly closed.

INACTIVE INGREDIENTS

Alcohol (60% v/v), propylene glycol, purified water

QUESTIONS

1-800-432-8534 (select option #2)

This Package Contains:

- One 60 mL (2 fl oz) bottle of Minoxidil Topical Solution 2% (one month supply)
- One child-resistant dropper applicator
- Information leaflet on how to use and obtain best results

Using the Dropper Applicator:

1. Remove cap by pushing and turning in direction of the arrows on the cap
2. Squeeze the rubber bulb and insert the dropper into the bottle. Release the bulb, allowing the dropper to fill to the 1 mL line. If the level of the solution is above the 1 mL line, squeeze the extra amount back into the bottle.
3. Place the tip near the part of the scalp you want to treat and gently squeeze the bulb to gradually release the solution. To prevent the solution from running off the scalp, apply a small amount at a time.
4. After each use attach the dropper to the bottle to make it child-resistant by turning it clockwise until tightly closed.

Minoxidil Topical Solution is for men who have a general thinning of hair on the top of the scalp (vertex) as shown. Minoxidil Topical Solution has been shown to regrow hair in men with the following degrees of thinning hair or hair loss.

If men have more hair loss than shown above, Minoxidil Topical Solution may not work.

*This product is not affiliated with, manufactured by, or produced by the makers of Rogaine®.

2004847 00660109I1 VC108596

Distributed by:

Actavis Mid Atlantic LLC

1877 Kawai Road

Lincolnton, NC 28092 USA

Made in Canada

Additional barcode labeling by:
Physicians Total Care, Inc.
Tulsa, Oklahoma 74146

PACKAGE LABEL.PRINCIPAL DISPLAY PANEL

Compare to the active ingredient in Men’s Rogaine®*

Regular Strength FOR MEN

HAIR REGROWTH TREATMENT

Minoxidil Topical Solution USP 2%

Clinically Proven to Help Regrow Hair

Revitalizes Hair Follicles

ONE MONTH SUPPLY 1-60 mL (2 fl oz) Bottle

ONE MONTH SUPPLY CARTON LABEL

CONSUMER INFORMATION

MINOXIDIL TOPICAL SOLUTION USP 2%

Important information about – Minoxidil Topical Solution USP 2% for Men

Save leaflet for future reference.

- Hair regrowth treatment

Minoxidil Topical Solution contains the only ingredient available without a prescription that is medically proven effective to help regrow hair.

Please read this leaflet carefully. It will help you understand how to use Minoxidil Topical Solution and what to expect from its use. If you have any questions after reading this leaflet, or anytime while using Minoxidil Topical Solution, you should ask your health care professional.

What is Minoxidil Topical Solution?

Minoxidil Topical Solution is a clear to pale yellow liquid medication for use only on the scalp to help regrow hair.

Who may use Minoxidil Topical Solution?

Minoxidil Topical Solution may be appropriate for you if you are an adult who is at least 18 years old and experiencing gradually thinning hair or gradual hair loss on the top of the head. The common hereditary thinning or hair loss process begins slowly and may become noticeable only after years of gradual loss.

Minoxidil Topical Solution is for men with hair loss or thinning that begins at the top of the scalp (vertex) as shown below. Frontal hair growth has not been demonstrated in clinical trials. Minoxidil Topical Solution is more likely to regrow hair in men with hair loss in the range shown below. If men have more hair loss than shown, Minoxidil Topical Solution may not work.

Many of those experiencing hair loss have other family members with gradual thinning hair or hair loss. If there is no family history of gradual thinning or gradual hair loss, or hair loss is patchy, talk to your doctor.

Who should NOT use Minoxidil Topical Solution?

Minoxidil Topical Solution will not prevent or improve hair loss which may occur with the use of some prescription and non-prescription medications, certain severe nutritional problems (very low body iron; excessive vitamin A intake), low thyroid states (hypothyroidism), chemotherapy, or diseases which cause scarring of the scalp. Also, Minoxidil Topical Solution will not improve hair loss due to:

- damage from the use of hair care products which cause scarring or deep burns of the scalp.
- hair grooming methods such as cornrowing or ponytails which require pulling the hair tightly back from the scalp.

You should ask your doctor if you are unsure of the cause for your hair loss.

Will Minoxidil Topical Solution work for me?

The amount of hair regrowth is different for each person. Not everyone will respond to Minoxidil Topical Solution. The response to Minoxidil Topical Solution cannot be predicted. No one will be able to grow back all their hair.

You may respond better if you have been losing your hair for a short period of time or have little initial hair loss.

In clinical studies of mostly white men aged 18-49 years with moderate degrees of hair loss, the following response of Minoxidil Topical Solution was reported:

Can Minoxidil Topical Solution be used to prevent hair loss?

We do not know if Minoxidil Topical Solution will prevent hair loss.

How soon can I expect results from using Minoxidil Topical Solution?

Since normal hair usually grows only ½ to 1 inch per month, hair regrowth with Minoxidil Topical Solution also takes time. Generally new hair growth is slow for a Minoxidil Topical Solution user. Continued use 2 times a day for at least 4 months is usually needed before you notice hair regrowth.

If you do not see hair regrowth in 4 months, stop using Minoxidil Topical Solution and see your doctor.

When you first begin to use Minoxidil Topical Solution, your hair loss may continue for up to 2 weeks. This hair loss is temporary. If you continue to lose hair after two weeks, see your doctor.

If Minoxidil Topical Solution is working, what will the hair look like?

At first, hair growth may be soft, downy, colorless hairs. After further use, the new hair should be the same color and thickness as the other hairs on your scalp.

How long do I need to use Minoxidil Topical Solution?

If you respond to Minoxidil Topical Solution, you will need to use it 2 times a day to keep and continue the hair regrowth. Up to 12 months of use may be needed to see your best results from Minoxidil Topical Solution.

What happens if I completely stop using Minoxidil Topical Solution? Will I keep the new hair?

Continuous use of Minoxidil Topical Solution is needed to maintain hair regrowth. If you stop using Minoxidil Topical Solution, the normal hair loss process will start again. You will probably lose your newly regrown hair in three to four months.

What is the dosage of Minoxidil Topical Solution?

You should apply a dose (1 mL) of Minoxidil Topical Solution directly onto the scalp in the hair loss area TWO TIMES A DAY; for example, once in the morning and once at night. Each bottle should last about one month, if used as directed. Please refer to the “Directions for Use” section of this leaflet.

What if I miss a dose or forget to use Minoxidil Topical Solution?

If you miss one or two daily doses of Minoxidil Topical Solution, just continue with your next dose. You should not make up for missed doses.

Can I use Minoxidil Topical Solution more than two times a day?

Will it work faster, better?

No. Minoxidil Topical Solution will not work faster or better if used more than 2 times a day. Studies have been carefully conducted to determine the correct amount of Minoxidil Topical Solution needed to get the best results. More frequent use or larger doses have not been shown to speed up hair growth and may increase your chance of side effects.

What are the most common side effects with Minoxidil Topical Solution?

The most common side effects are itching and other skin irritations of the treated area of the scalp. Minoxidil Topical Solution contains alcohol, which would cause burning or irritation of the eyes or sensitive skin areas. If Minoxidil Topical Solution accidentally gets into these areas, rinse with large amounts of cool tap water. Contact your doctor if irritation persists.

What kind of shampoo should I use with Minoxidil Topical Solution?

If you wash your scalp before applying Minoxidil Topical Solution, use a mild shampoo.

Can I use hair sprays, mousses, conditioners, gels, etc.?

Yes. There is no need to change your usual hair care routine when using Minoxidil Topical Solution. However, you should apply Minoxidil Topical Solution first and wait for it to dry before applying your styling aids.

Can I have my hair colored or permed or use hair relaxers while using Minoxidil Topical Solution?

Yes. We have no information that these treatments change the effect of Minoxidil Topical Solution. However, to avoid possible scalp irritation, you should make sure all of the Minoxidil Topical Solution has been washed out of the hair and scalp before using these chemicals.

Can I apply Minoxidil Topical Solution and wash my hair an hour later?

No. For Minoxidil Topical Solution to work best, you should allow Minoxidil Topical Solution to remain on the scalp for about 4 hours before washing.

Can I go swimming or out in the rain?

Yes. Avoid washing off the Minoxidil Topical Solution. If possible, apply Minoxidil Topical Solution to a dry scalp after swimming, or wait about 4 hours after application before going swimming. Do not let your scalp get wet from the rain after applying Minoxidil Topical Solution.

Can Minoxidil Topical Solution produce unwanted hair?

Although unwanted hair growth has been reported on the face and on other parts of the body, such reports have been infrequent. The unwanted hair growth may be caused by the transfer of Minoxidil Topical Solution to areas other than the scalp, or by absorption into the circulatory system of low levels of the active ingredient, or by a medical condition not related to the use of Minoxidil Topical Solution.

If you experience unwanted hair, discontinue using Minoxidil Topical Solution and see your doctor for recommendations about appropriate treatment. After stopping use of Minoxidil Topical Solution, the unwanted hair, if caused by the use of Minoxidil Topical Solution, should go away over time.

You can take steps to decrease the chances of unwanted hair growth: 1) limit the application of Minoxidil Topical Solution only to the scalp; 2) if you use your hands to apply Minoxidil Topical Solution, wash your hands thoroughly afterwards; and 3) allow sufficient drying time (usually 2 to 4 hours before going to bed) after your nighttime application of Minoxidil Topical Solution.

Can I use Minoxidil Topical Solution for baldness or hair loss in babies and children?

No. Minoxidil Topical Solution must not be used to treat baldness or hair loss in babies or children.

Are there any special warnings about the use of Minoxidil Topical Solution?

For external use only

Flammable: Keep away from fire or flame

Do not use if

- your degree of hair loss is more than that shown on the front of this leaflet, because this product may not work for you.
- you have no family history of hair loss
- your hair loss is sudden and/or patchy
- you do not know the reason for your hair loss
- you are under 18 years of age. Do not use on babies and children.
- your scalp is red, inflamed, infected, irritated, or painful
- you use other medicines on the scalp

Ask a doctor before use if you have heart disease.

When using this product

- do not apply on other parts of the body
- avoid contact with the eyes. In case of accidental contact, rinse eyes with large amounts of cool tap water.
- some people have experienced changes in hair color and/or texture
- it takes time to regrow hair. You may need to use this product 2 times a day for at least 4 months before you see results.
- the amount of hair regrowth is different for each person. This product will not work for everyone.

Stop use and ask a doctor if

- chest pain, rapid heartbeat, faintness, or dizziness occurs
- sudden, unexplained weight gain occurs
- your hands or feet swell
- scalp irritation or redness occurs
- unwanted facial hair growth occurs
- you do not see hair regrowth in 4 months

Keep out of reach of children. If swallowed, get medical help or contact a Poison Control Center right away.

What factors may increase the risk of serious side effects with Minoxidil Topical Solution?

Minoxidil Topical Solution should be applied only to the scalp. The risk of side effects may be greater when it is applied to other parts of the body.

Directions for Use

1. Remove the cap. To remove, push down and turn in direction of the arrows on the cap.
2. Part your hair in the area of hair thinning/loss. Follow the instructions below for using the dropper applicator and apply one mL 2 times a day directly onto the scalp in the hair loss area. Do not use more. Spread the liquid evenly over the hair loss area. If you use your fingers, wash hands with soap and water immediately. Each bottle should last about one month, if used as directed. Use a mild shampoo if you wash your scalp before applying Minoxidil Topical Solution.

Using the Dropper Applicator

1. Squeeze the rubber bulb and insert the dropper into the bottle. Release the bulb, allowing the dropper to fill to the 1 mL line. If the level of the solution is above the 1 mL line, squeeze the extra amount back into the bottle.
2. Next, place the tip near the part of the scalp you want to treat and gently squeeze the bulb to gradually release the solution. To prevent the solution from running off the scalp, apply a small amount at a time.
3. After each use attach the dropper to the bottle to make it child-resistant by turning it clockwise until tightly closed.

If you have any other questions, ask your health care professional.

Store at Controlled Room Temperature 20º to 25ºC (68º to 77ºF). Keep tightly closed.

Save this leaflet for future reference.

Manufactured by: Contract Pharmaceuticals Ltd.

7600 Danbro Crescent

Mississauga, ON

Canada, L5N 6L6

For: Actavis Mid Atlantic LLC

1877 Kawai Road

Lincolnton, NC 28092 USA

FORM NO. 0066 Rev. 1/08

2004373 VC3043